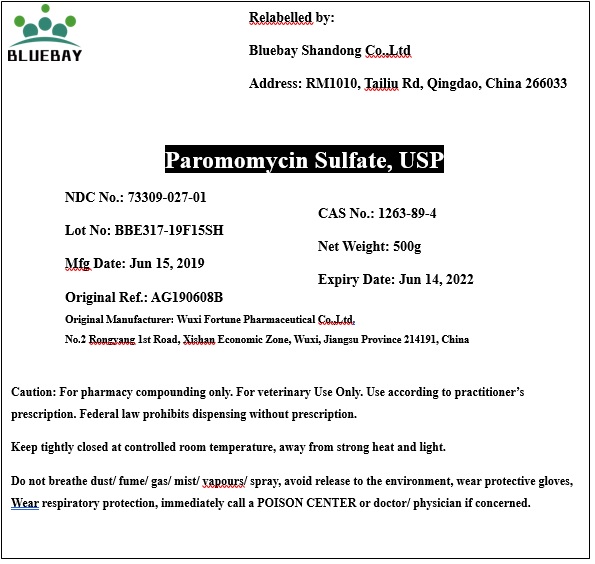 DRUG LABEL: Paromomycin Sulfate
NDC: 73309-027 | Form: POWDER
Manufacturer: BLUEBAY SHANDONG CO.,LTD
Category: other | Type: BULK INGREDIENT
Date: 20190911

ACTIVE INGREDIENTS: PAROMOMYCIN SULFATE 1 g/1 g

Paromomycin Sulfate